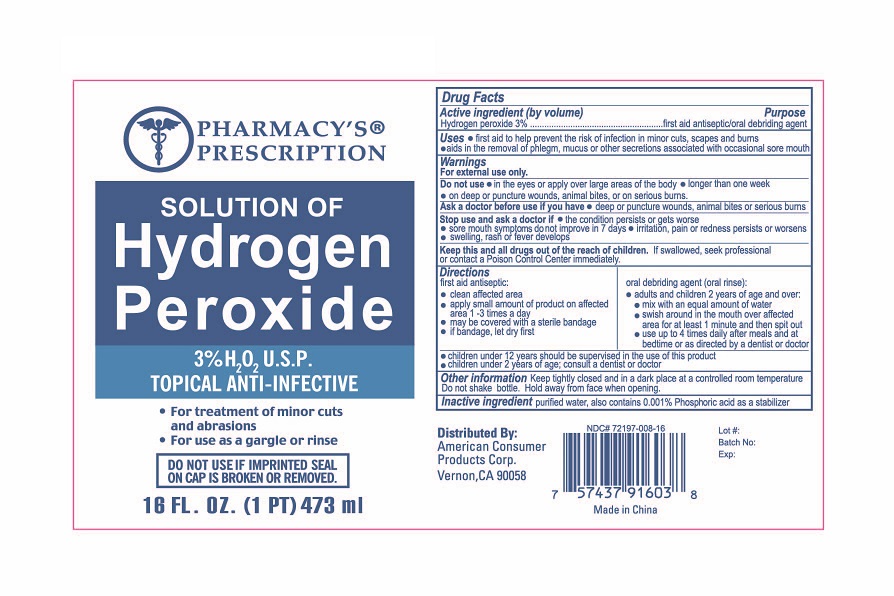 DRUG LABEL: PHARMACYS PRESCRIPTION HYDROGEN PEROXIDE
NDC: 72197-008 | Form: LIQUID
Manufacturer: American Consumer Products Corp
Category: otc | Type: HUMAN OTC DRUG LABEL
Date: 20180807

ACTIVE INGREDIENTS: HYDROGEN PEROXIDE 3 mL/1 mL
INACTIVE INGREDIENTS: WATER; PHOSPHORIC ACID

Pharmacy's Prescription 16OZ Hydrogen Peroxide

Active Ingredient

Active ingredient (by volume)

Hydrogen peroxide 3%

Purpose

First aid antiseptic/oral debriding agent.

Warnings

For external use only.

Stop Use

Stop use and ask a doctor if: the condition persists or gets worse, sore mouth symptoms do not improve within 7 days, irritation, pain or redness persists or worsens, swelling, rash or fever develops.

Keep out of reach of children

Keep this and all drugs out of the reach of children. If swallowed, seek professional or contact a Poison Control Center immediately.

Directions

First aid antiseptic:

Clean affected area; apply small amount of product on affected area 1-3 times a day; may be covered with a sterile bandage; if bandage, let dry first.

Oral debriding agent (oral rinse):

Adults and children 2 years of age and over:

Mix with an equal amount of water; swish around in the mouth over affected area for at least 1 minute and then spit out; use up to 4 times daily after meals and at bedtime or as directed by a dentist or doctor.

Inactive Ingredients

Inactive ingredient

Purified water, also contains 0.001% Phosphoric acid as a stabilizer.

Indications & Usage Section

Do not use

In the eyes or apply over large areas of the body; longer than one week; on deep or puncture wounds, animal bites, or on serious burns.